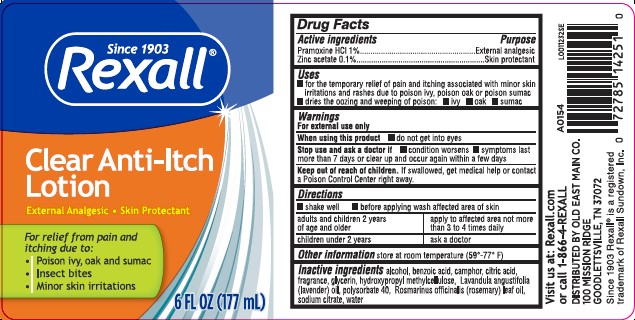 DRUG LABEL: Clear Anti-Itch
NDC: 55910-218 | Form: LOTION
Manufacturer: Old East Main Co.
Category: otc | Type: HUMAN OTC DRUG LABEL
Date: 20260302

ACTIVE INGREDIENTS: PRAMOXINE HYDROCHLORIDE 10 mg/1 mL; ZINC ACETATE 1 mg/1 mL
INACTIVE INGREDIENTS: ALCOHOL; BENZOIC ACID; CAMPHOR (SYNTHETIC); CITRIC ACID MONOHYDRATE; GLYCERIN; HYPROMELLOSE, UNSPECIFIED; LAVENDER OIL; POLYSORBATE 40; ROSEMARY OIL; SODIUM CITRATE; WATER

Rexall 218.002/218AF
Clear Itch Relief Lotion

Active ingredients

Pramoxine HCl 1%

Zinc acetate 0.1%

Purpose

External analgesic

Skin protectant

Uses

- for the temporary relief of pain and itching associated with minor skin irritations and rashes due to poison ivy, poison oak or poison sumac
- dries the oozing and weeping of poison: - ivy - oak - sumac

Warnings

For external use only

When using this product

- do not get into eyes

Stop use section and ask a doctor if

- condition worsens
- symptoms last more than 7 days or clear up and occur again within a few days

Keep out of reach of children.

If swallowed, get medical help or contact a Poison Control Center right away.

Directions

- shake well
- before applying wash affected area of skin

adults and children 2 years of age and older - apply to affected area not more than 3 to 4 times daily

children under 2 years - ask a doctor

Other information

store at room temperature (59° - 77°F)

Inactive ingredients

alcohol, benzoic acid, camphor, citric acid, fragrance, glycerin, hydroxypropyl methylcellulose, Lavandula angustifolia (lavender) oil, polysorbate 40, Rosmarinus officinalis (rosemary) leaf oil, sodium citrate, water

Adverse reaction

Visit us at: Rexall.com or call 1-866-4-REXALL

DISTRIBUTED BY OLD EAST MAIN CO.

100 Mission Ridge

Goodlettsville, TN 37072

Since 1903 Rexall®is a registered trademark of Rexall Sundown, Inc.

A0154

principal display panel

Since 1903

Rexall®

Clear Anti-Itch Lotion

External Analgesic • Skin Protectant

For relief from pain and itching due to:

- Poison ivy, oak and sumac
- Insect bites
- Minor skin irritations

6 FL OZ (177 mL)